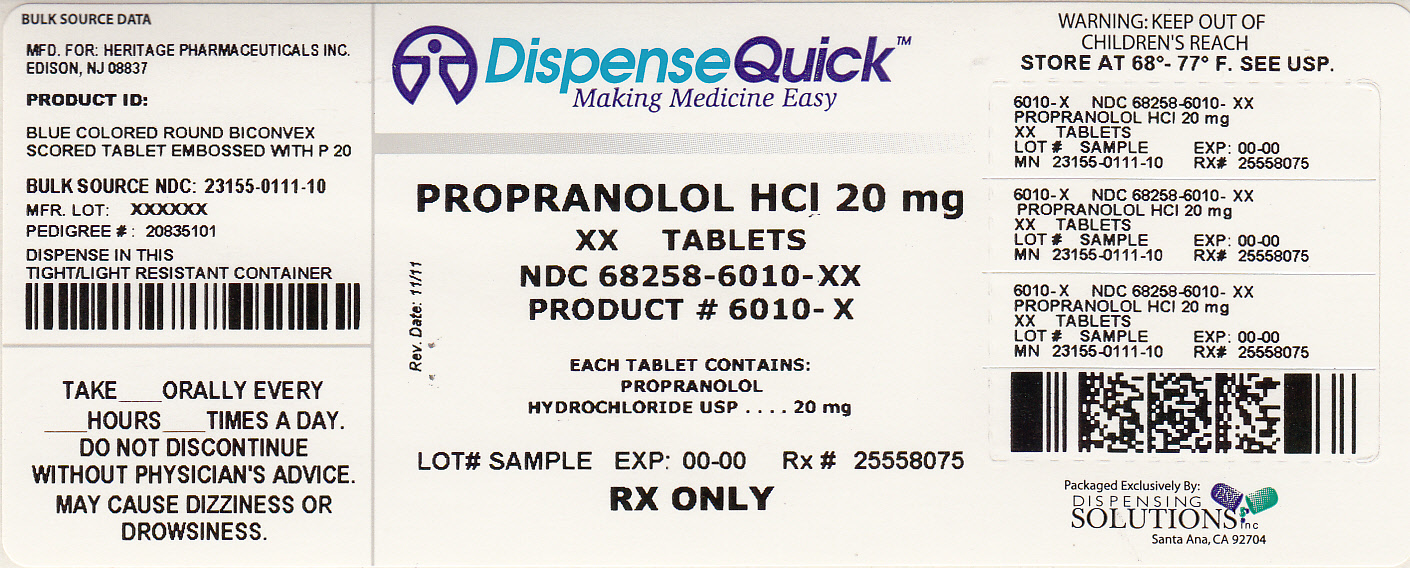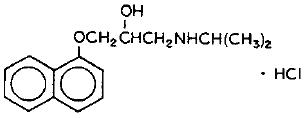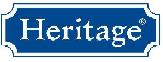 DRUG LABEL: Propranolol Hydrochloride
NDC: 68258-6010 | Form: TABLET
Manufacturer: Dispensing Solutions, Inc.
Category: prescription | Type: HUMAN PRESCRIPTION DRUG LABEL
Date: 20120216

ACTIVE INGREDIENTS: PROPRANOLOL HYDROCHLORIDE 20 mg/1 1
INACTIVE INGREDIENTS: FD&C BLUE NO. 1; LACTOSE MONOHYDRATE; MAGNESIUM STEARATE; POVIDONE; SODIUM STARCH GLYCOLATE TYPE A POTATO; STARCH, CORN

Propranolol Hydrochloride Tablets, USP

Rx Only

DESCRIPTION

hydrochloride(Propranolol is a synthetic beta-adrenergic receptor blocking agent chemically described as 2-Propanol, 1-[(1-methylethyl)amino]-3-(1-naphthalenyloxy)-, hydrochloride,(±)-. It’s molecular and structural formulae are:

Propranolol hydrochloride is a stable, white, crystalline solid which is readily soluble in water and in ethanol. Its molecular weight is 295.80.
Propranolol hydrochloride tablets, USP are available as 10 mg, 20 mg, 40 mg, 60 mg, and 80 mg tablets for oral administration.
The inactive ingredients contained in propranolol hydrochloride tablets, USP are: lactose monohydrate, corn starch, sodium starch glycolate, magnesium stearate, and povidone. In addition, propranolol hydrochloride tablets, USP 10 mg, 40 mg and 80 mg contain and C yellow No.6 Aluminium Lake and Color D and C Yellow No. 10; propranolol hydrochloride tablets, USP 20 mg and 40mg contain FD and C Blue No.1 and propranolol hydrochloride tablets, USP 60 mg contain D and C Red No. 30 Lake.

CONTRAINDICATIONS

Propranolol is contraindicated in 1) cardiogenic shock; 2) sinus bradycardia and greater than first degree block; 3) bronchial asthma; and 4) in patients with known hypersensitivity to propranolol hydrochloride.

ADVERSE REACTIONS

The following adverse events were observed and have been reported in patients using propranolol.

Cardiovascular: Bradycardia; congestive heart failure; intensification of AV block; hypotension; paresthesia of hands; thrombocytopenic purpura; arterial insufficiency, usually of the Raynaud type.

Central Nervous System: Lightheadedness, mental depression manifested by insomnia, lassitude, weakness, fatigue; catatonia; visual disturbances; hallucinations; vivid dreams; an acute reversible syndrome characterized by disorientation for time and place, short-term memory loss, emotional lability, slightly clouded sensorium, and decreased performance on neuropsychometrics. For immediate-release formulations, fatigue, lethargy, and vivid dreams appear dose-related.

Gastrointestinal: Nausea, vomiting, epigastric distress, abdominal cramping, diarrhea, constipation, mesenteric arterial thrombosis, ischemic colitis.

Allergic: Hypersensitivity reactions, including anaphylactic/anaphylactoid reactions, pharyngitis and agranulocytosis; erythematous rash, fever combined with aching and sore throat; laryngospasm, and respiratory distress.

Respiratory: Bronchospasm.

Hematologic: Agranulocytosis, nonthrombocytopenic purpura, thrombocytopenic purpura.

Autoimmune: Systemic lupus erythematosus (SLE).

Skin and mucous membranes: Stevens-Johnson Syndrome, toxic epidermal necrolysis, dry eyes, exfoliative dermatitis, erythema multiforme, urticaria, alopecia, SLE-like reactions, and psoriasiform rashes. Oculomucocutaneous syndrome involving the skin, serous membranes and conjunctivae reported for a beta-blocker (practolol) have not been associated with propranolol.

Genitourinary: Male impotence; Peyronie’s disease.

OVERDOSAGE

Propranolol is not significantly dialyzable. In the event of overdosage or exaggerated response, the following measures should be employed:

General: If ingestion is or may have been recent, evacuate gastric contents, taking care to prevent pulmonary aspiration.

Supportive Therapy: Hypotension and bradycardia have been reported following propranolol overdose and should be treated appropriately. Glucagon can exert potent inotropic and chronotropic effects and may be particularly useful for the treatment of hypotension or depressed myocardial function after a propranolol overdose. Glucagon should be administered as 50-150 mcg/kg intravenously followed by continuous drip of 1-5 mg/hour for positive chronotropic effect. Isoproterenol, dopamine or phosphodiesterase inhibitors may also be useful. Epinephrine, however, may provoke uncontrolled hypertension. Bradycardia can be treated with atropine or isoproterenol. Serious bradycardia may require temporary cardiac pacing.

The electrocardiogram, pulse, blood pressure, neurobehavioral status and intake and output balance must be monitored. Isoproterenol and aminophylline may be used for bronchospasm.

HOW SUPPLIED

Propranolol hydrochloride tablets, USP are supplied as follows:

10mg: Each tablet is an orange colored, round, biconvex tablet, embossed with "P" and "10" on either side of the breakline on one side and plain on the other side.

Each 10 mg tablet contains 10 mg propranolol hydrochloride USP and is supplied in the following packages sizes:

Bottles of 30 tablets NDC 23155-110-03

Bottles of 60 tablets NDC 23155-110-06

Bottles of 100 tablets NDC 23155-110-01

Bottles of 500 tablets NDC 23155-110-05

Bottles of 1000 tablets NDC 23155-110-10

20mg: Each tablet is a blue colored, round, biconvex tablet, embossed with "P" and "20" on either side of the breakline on one side and plain on the other side.

Each 20 mg tablet contains 20 mg of propranolol hydrochloride USP and is supplied in the following package sizes:

Bottles of 30 tablets NDC 23155-111-03

Bottles of 60 tablets NDC 23155-111-06

Bottles of 100 tablets NDC 23155-111-01

Bottles of 500 tablets NDC 23155-111-05

Bottles of 1000 tablets NDC 23155-111-10

40mg: Each tablet is a green colored, round, biconvex tablet, embossed with "P" and "40"on either side of the breakline on one side and plain on the other side.

Each 40 mg tablet contains 40 mg of propranolol hydrochloride USP and is supplied in the following package sizes:

Bottles of 30 tablets NDC 23155-112-03

Bottles of 60 tablets NDC 23155-112-06

Bottles of 100 tablets NDC 23155-112-01

Bottles of 500 tablets NDC 23155-112-05

Bottles of 1000 tablets NDC 23155-112-10

60mg: Each tablet is a pink colored, round, biconvex tablet, embossed with "P" and "60" on either side of the breakline on one side and plain on the other side.

Each 60 mg tablet contains 60 mg of propranolol hydrochloride USP and is supplied in the following package sizes:

Bottles of 30 tablets NDC 23155-113-03

Bottles of 60 tablets NDC 23155-113-06

Bottles of 100 tablets NDC 23155-113-01

Bottles of 500 tablets NDC 23155-113-05

Bottles of 1000 tablets NDC 23155-113-10

80mg: Each tablet is a yellow colored, round, biconvex tablet, embossed with "P" and "80" on either side of the breakline on one side and plain on the other side.

Each 80 mg tablet contains 80 mg of propranolol hydrochloride USP and is supplied in the following package sizes:

Bottles of 30 tablets NDC 23155-114-03

Bottles of 60 tablets NDC 23155-114-06

Bottles of 100 tablets NDC 23155-114-01

Bottles of 500 tablets NDC 23155-114-05

Bottles of 1000 tablets NDC 23155-114-10

Storage: Store at 20°-25°C (68-(°77(°F); excursions permitted to 15°-30(°C (59(°-86(°F) [see USP Controlled Room Temperature]

Protect from light.

Dispense in a well closed, light-resistant container as defined in USP.

Call your doctor for medical advice about side effects. You may report side effects to FDA at 1-800-FDA-1088.

Manufactured for:

Heritage Pharmaceuticals Inc.

Edison, NJ 08837

1.866.901.DRUG (3784)

Manufactured by:

Ipca Laboratories Limited

48, Kandivli Ind. Estate,

Mumbai 400 067, India.

Iss. 0109

PRINCIPAL DISPLAY PANEL

NDC 68258-6010-XX

NDC 68258-6010-03

NDC 68258-6010-09